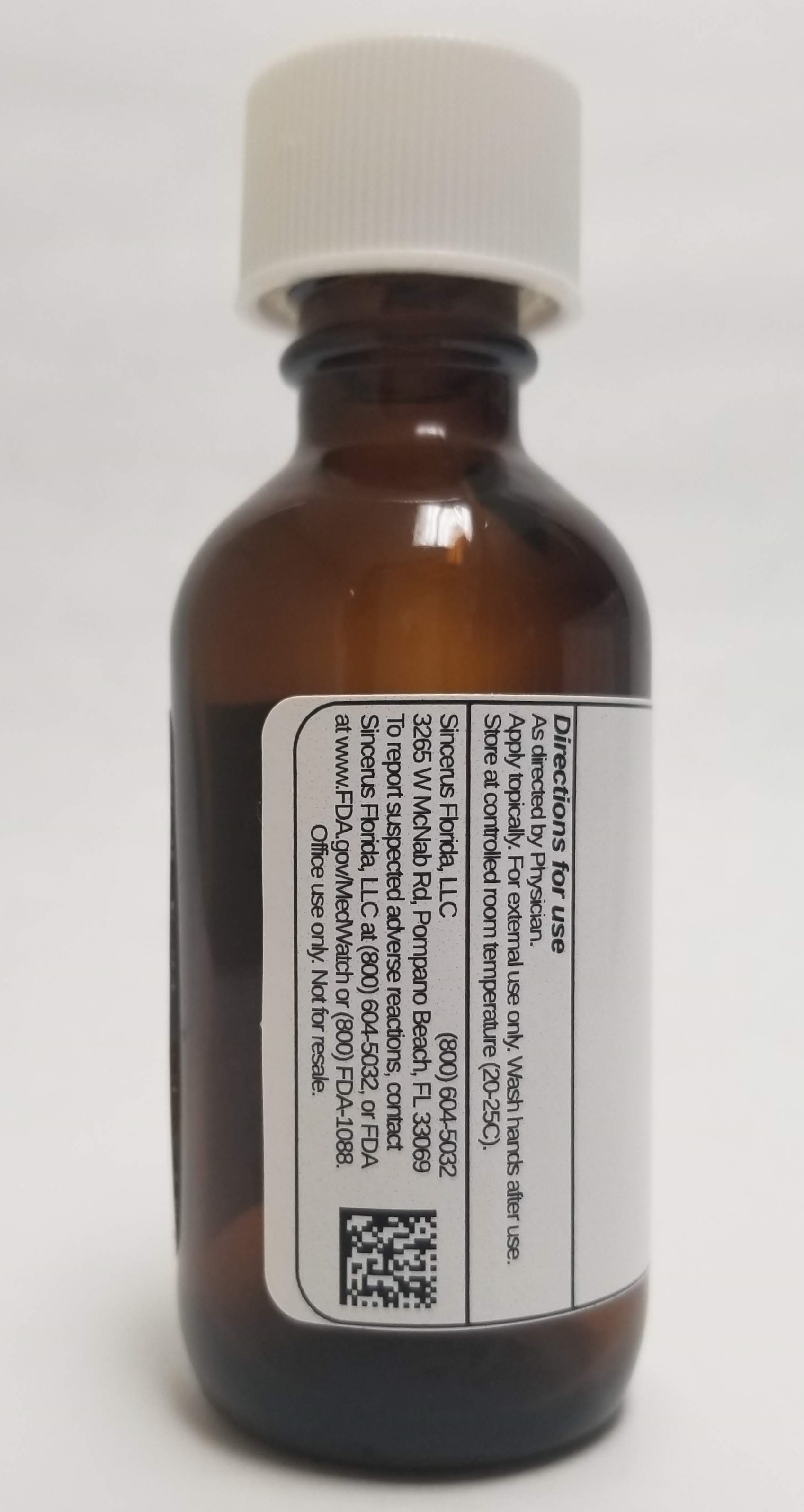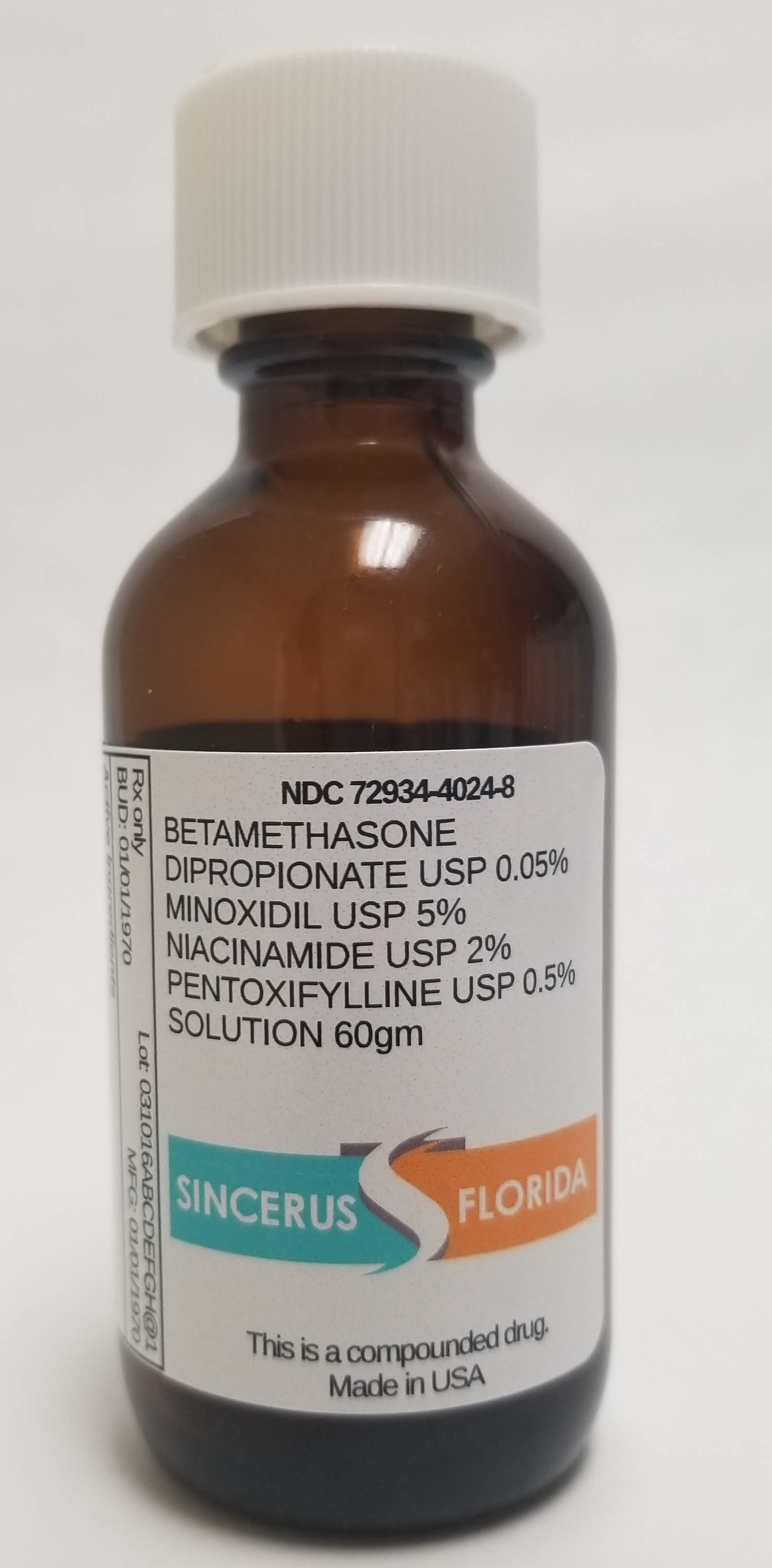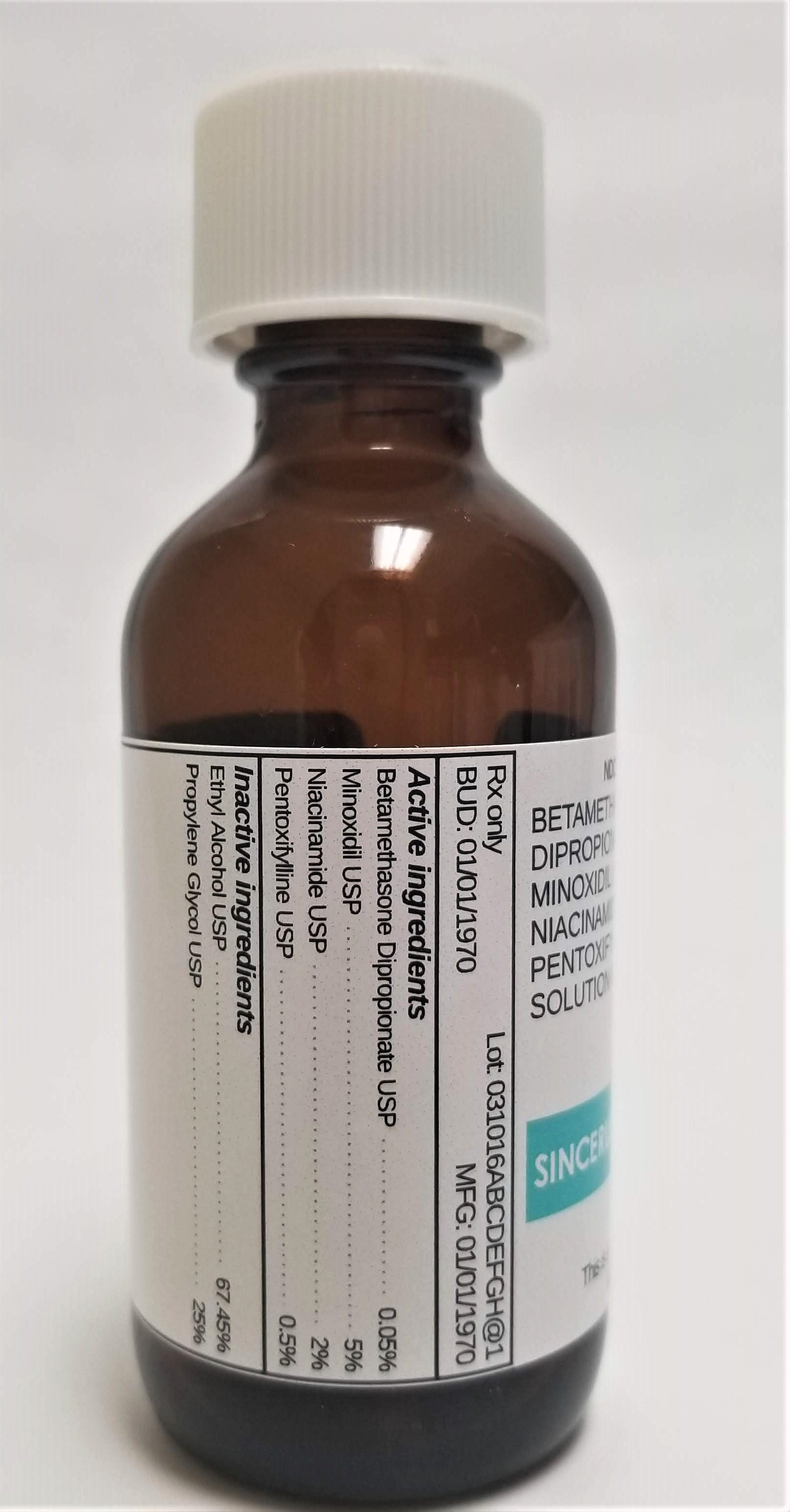 DRUG LABEL: BETAMETHASONE DIPROPIONATE 0.05% / MINOXIDIL 5% / NIACINAMIDE 2% / PENTOXIFYLLINE 0.5%
NDC: 72934-4024 | Form: SOLUTION
Manufacturer: Sincerus Florida, LLC
Category: prescription | Type: HUMAN PRESCRIPTION DRUG LABEL
Date: 20190508

ACTIVE INGREDIENTS: PENTOXIFYLLINE 2 g/100 g; BETAMETHASONE DIPROPIONATE 0.05 g/100 g; MINOXIDIL 5 g/100 g; NIACINAMIDE 2 g/100 g

BETAMETHASONE DIPROPIONATE 0.05% / MINOXIDIL 5% / NIACINAMIDE 2% / PENTOXIFYLLINE 0.5%